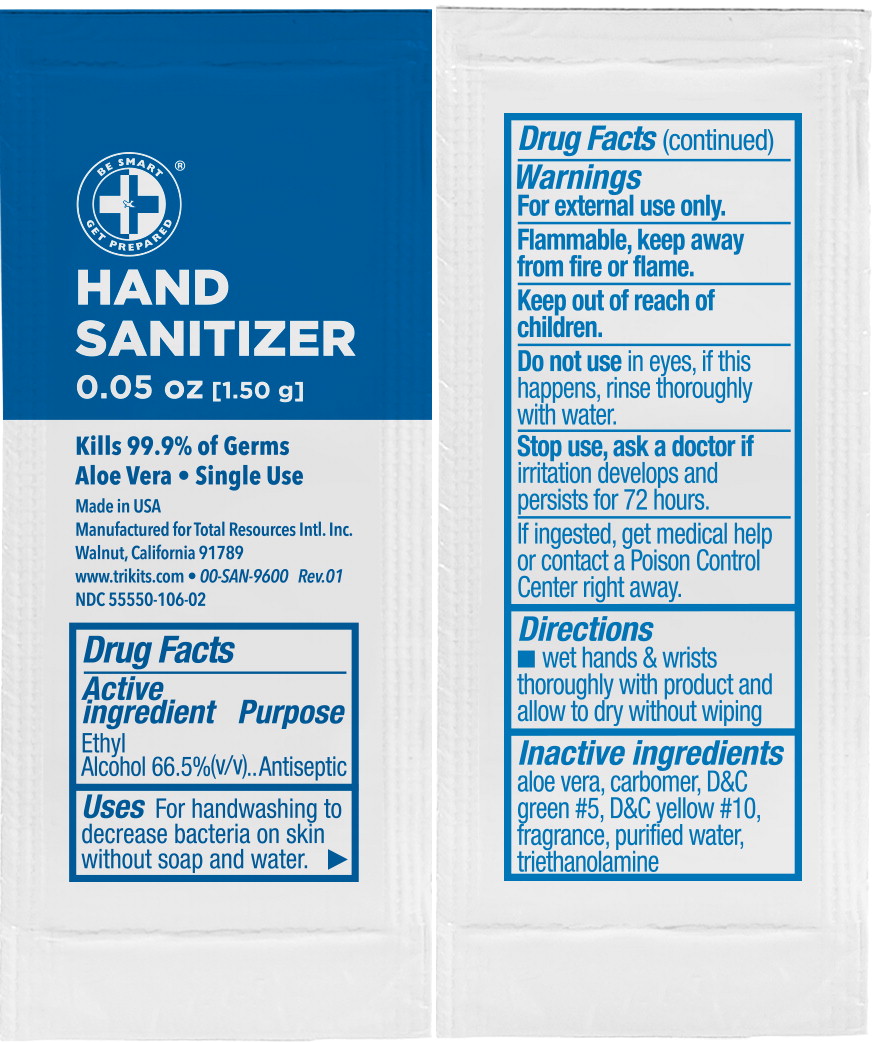 DRUG LABEL: Be Smart Get Prepared Hand Sanitizer
NDC: 55550-106 | Form: GEL
Manufacturer: Total Resources International, Inc
Category: otc | Type: HUMAN OTC DRUG LABEL
Date: 20240702

ACTIVE INGREDIENTS: ALCOHOL 0.665 mL/1 mL
INACTIVE INGREDIENTS: ALOE; CARBOMER INTERPOLYMER TYPE A (ALLYL SUCROSE CROSSLINKED); D&C GREEN NO. 5; D&C YELLOW NO. 10; TROLAMINE; WATER

Drug Facts

Active ingredient

Ethyl Alcohol 66.5%(v/v)

Purpose

Antiseptic

Uses

For handwashing to decrease bacteria on skin without soap and water.

Warnings

For external use only.

Flammable, keep away from fire or flame.

Keep out of reach of children.

Do not use in eyes, if this happens, rinse thoroughly with water.

Stop use, ask a doctor if irritation develops and persists for 72 hours.

If ingested, get medical help or contact a Poison Control Center right away.

Directions

- wet hands & wrists thoroughly with product and allow to dry without wiping

Inactive ingredients

aloe vera, carbomer, D&C green #5, D&C yellow #10, fragrance, purified water, triethanolamine

Principal Display Panel – 1 mL Pouch Label

BE SMART

GET PREPARED®

HAND SANITIZER

0.05 oz [1.50 g]

Kills 99.9% of Germs

Aloe Vera • Single Use

Made in USA

Manufactured for Total Resources Intl. Inc

Walnut, California 91789

www.trikits.com • 00-SAN-9600 Rev.01

NDC 55550-106-02